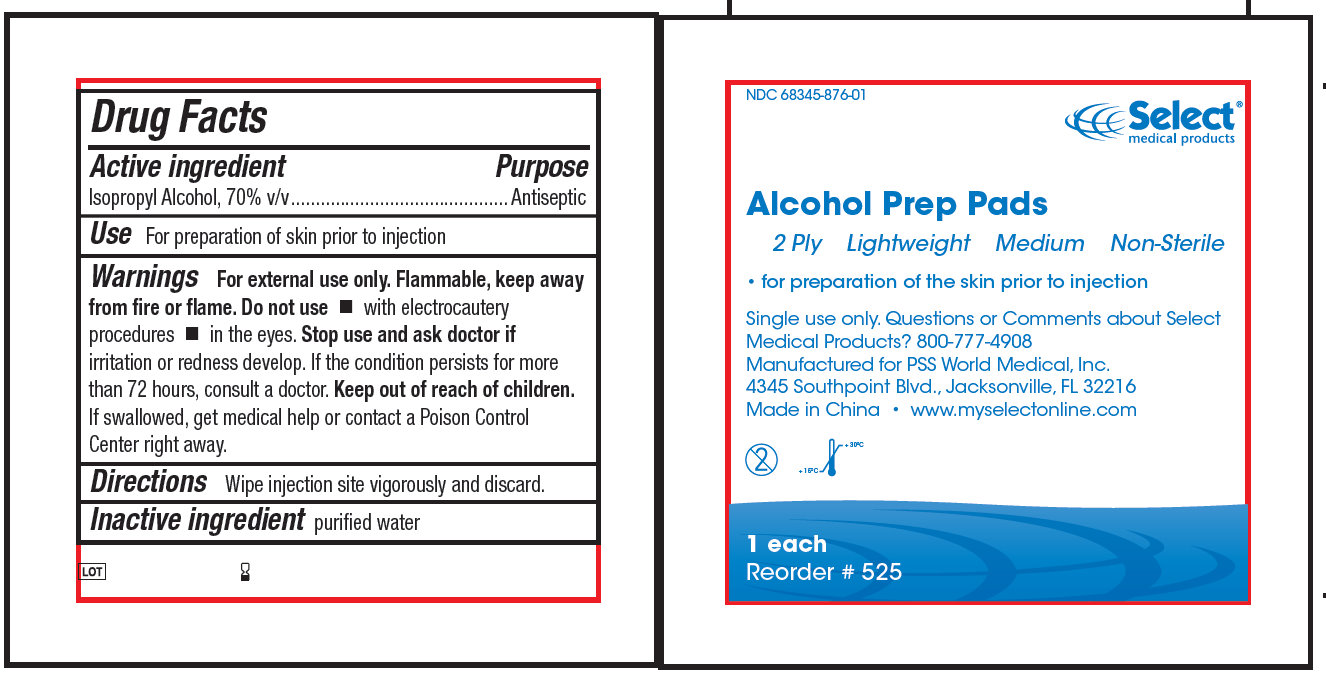 DRUG LABEL: Alcohol Prep Pads Lightweight Non-Sterile
NDC: 68345-876 | Form: LIQUID
Manufacturer: PSS World Medical
Category: otc | Type: HUMAN OTC DRUG LABEL
Date: 20100903

ACTIVE INGREDIENTS: ISOPROPYL ALCOHOL 70 g/100 g
INACTIVE INGREDIENTS: WATER

Alcohol Prep Pads - Lightweight Non-Sterile

Active ingredient

Isopropyl Alcohol, 70 % v/v

Purpose

Antiseptic

INDICATIONS AND USAGE

Use For preparation of the skin prior to an injection

Warnings

For external use only.

Flammable, keep away from fire or flame.

Do not use

- with electrocautery procedures
- in the eyes

Stop use and ask a doctor If irritation and redness develop. If condition persists for more than 72 hours, consult a doctor.

Keep out of reach of children. If swallowed, get medical help or contact a Poison Control Center right away.

Directions

- Wipe injection site vigorously and discard.

Inactive ingredient Purified water

Questions or Comments about Select Medical Products? 800-777-4908

DESCRIPTION

Manufactured for PSS World Medical, Inc.

4345 Southpoint Blvd., Jacksonville, FL 32216

Made in China www.myselectonline.com

PACKAGE LABEL

NDC 68345-876-01
Select medical products
Alcohol Prep Pads
2 Ply Lightweight Medium Non-Sterile

- for preparation of the skin prior to injection

Single use only. Questions or Comments about Select Medical Products? 800-777-4908
Manufactured for PSS World Medical, Inc.
4345 Southpoint Blvd., Jacksonville, FL 32216
Made in China www.myselectonline.com
1 each
Reorder number 525